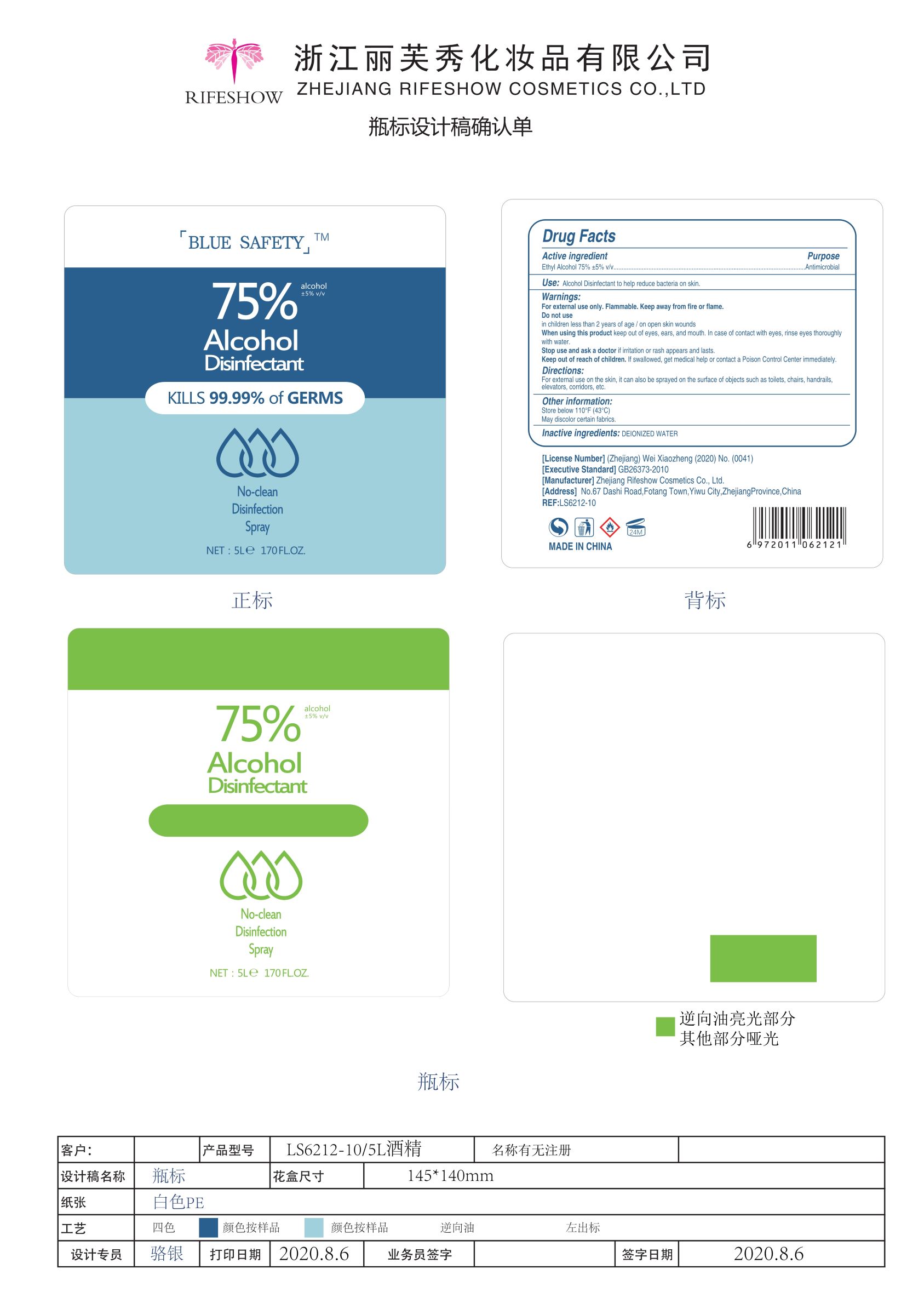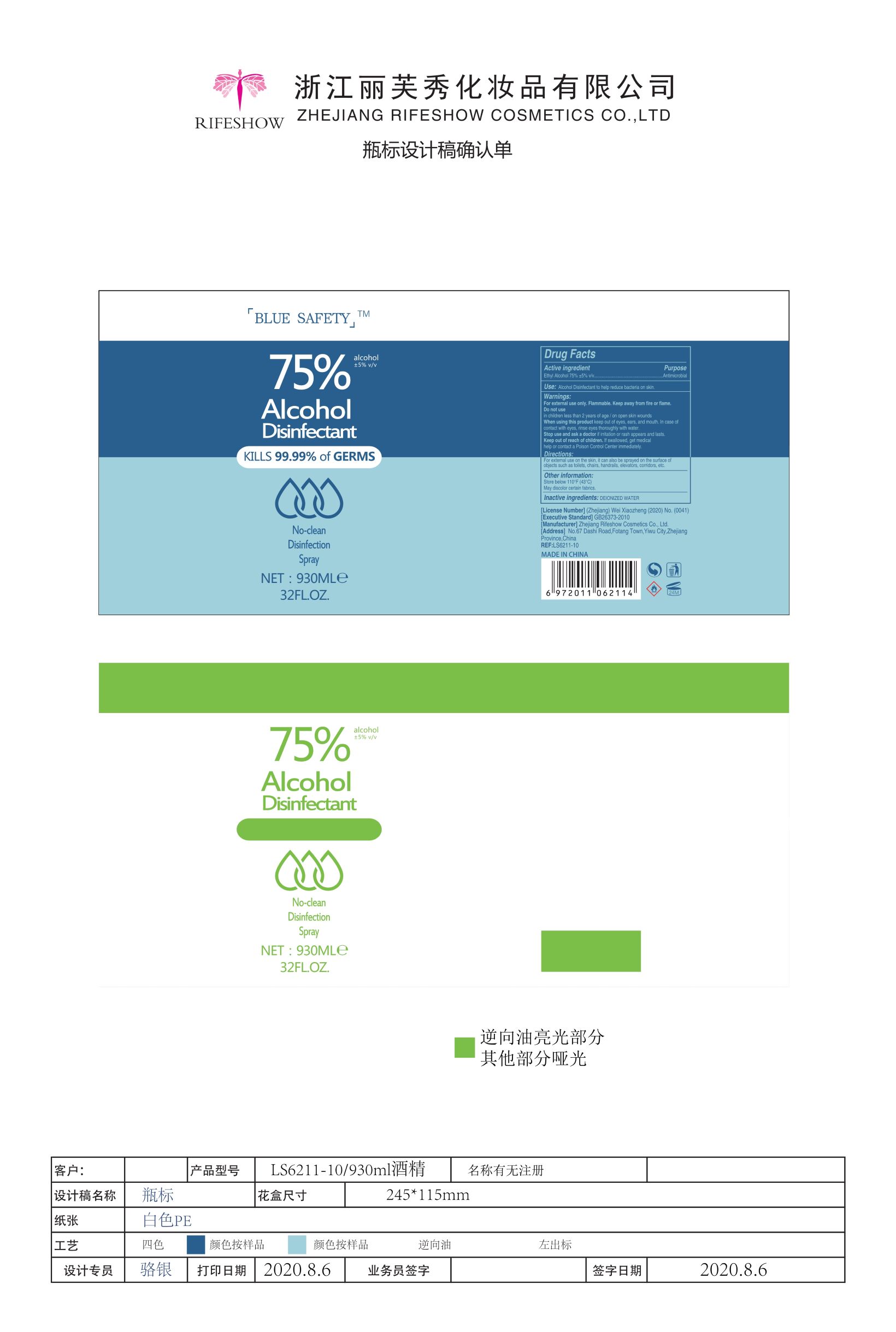 DRUG LABEL: Alcohol Disinfectant
NDC: 56084-025 | Form: LIQUID
Manufacturer: Zhejiang RIFESHOW Cosmetics Co., Ltd.
Category: otc | Type: HUMAN OTC DRUG LABEL
Date: 20200811

ACTIVE INGREDIENTS: ALCOHOL 75 mL/100 mL
INACTIVE INGREDIENTS: WATER

Zhejiang RIFESHOW Cosmetics Co., Ltd.
Alcohol Disinfectant
930mL （56084-025-01）
5L （56084-025-02）

Active Ingredient(s)

Ethyl Alcohol 75%±5% v/v

Purpose

Antimicrobial

Use

Alcohol Disinfectant to help reduce bacteria on skin.

Warnings

- For external use only.
- Flammable. Keep away from fire or flame.

Do not use

- in children less than 2 years of age
- on open skin wounds

When using this product keep out of eyes, ears, and mouth. In case of contact with eyes, rinse eyes thoroughly with water.

Stop use and ask a doctor if irritation or rash appears and lasts.

KEEP OUT OF REACH OF CHILDREN

If swallowed, get medical help or contact a Poison Control center immediately.

Directions

For external use on the skin, it can also be sprayed on the surface of objects such as toilets, chairs, handrails, elevators, corridors, etc.

Other information

- Store below 110℉(43℃)
- May discolor certain fabrics.

Inactive ingredients

DEIONIZED WATER

Package Label - Principal Display Panel

930 mL NDC: 56084-025-01

5000 mL NDC: 56084-025-02